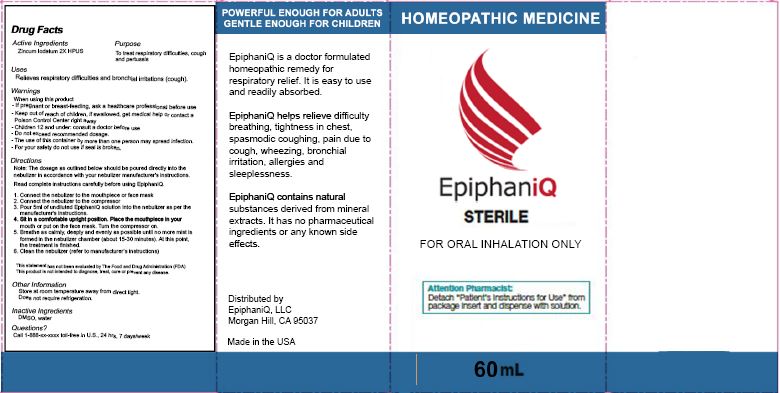 DRUG LABEL: EpiphaniQ Sterile

NDC: 79813-203 | Form: INHALANT
Manufacturer: EpiphaniQ LLC
Category: homeopathic | Type: HUMAN OTC DRUG LABEL
Date: 20211229

ACTIVE INGREDIENTS: ZINC IODIDE 2 [hp_X]/100 mL
INACTIVE INGREDIENTS: DIMETHYL SULFOXIDE; WATER

EpiphaniQ Nebulizer Solution (79813-203)

ACTIVE INGREDIENT

ZINCUM IODATUM 2X HPUS

PURPOSE

TO TREAT RESPIRATORY DIFFICULTIES, COUGH AND PERTUSSIS

USES

Relieves respiratory difficulties and bronchial irritations (cough).

WARNINGS

When using this product

- If pregnant or breast-feeding ask a healthcare professional before use
- Children under 12: consult a doctor before use
- Do not exceed recommended dosage
- The use of this container by more than one person may spread infection
- For your safety do not use if seal is broken

- Keep out of reach of children. In case of overdose, get medical help or contact a Poison Control center right away

DIRECTIONS

Note: The dosage as outlined below should be poured directly into the nebulizer in accordance with your nebulizer manufacturer's instructions.

Read complete instructions carefully before using EpiphaniQ.

1. Connect the nebulizer to the mouthpiece or face mask
2. Connect the nebulizer to the compressor
3. Pour 5ml of undiluted EpiphaniQ solution into the nebulizer as per the manufacturer's instructions.
4. Sit in a comfortable upright position. Place the mouthpiece in your mouth or put on the face mask. Turn the compressor on.
5. Breathe as calmly, deeply and evenly as possible until no more mist is formed in the nebulizer chamber (about 15-30 minutes). At this point,
the treatment is finished.
6. Clean the nebulizer (refer to manufacturer’s instructions)

Other Information

Store at room temperature away from direct light. Does not require refrigeration.

INACTIVE INGREDIENTS

DMSO, WATER

QUESTIONS

CALL TOLL FREE 1-800-XXX-XXXX IN THE U.S., 24 HRS, 7 DAY/WEEK